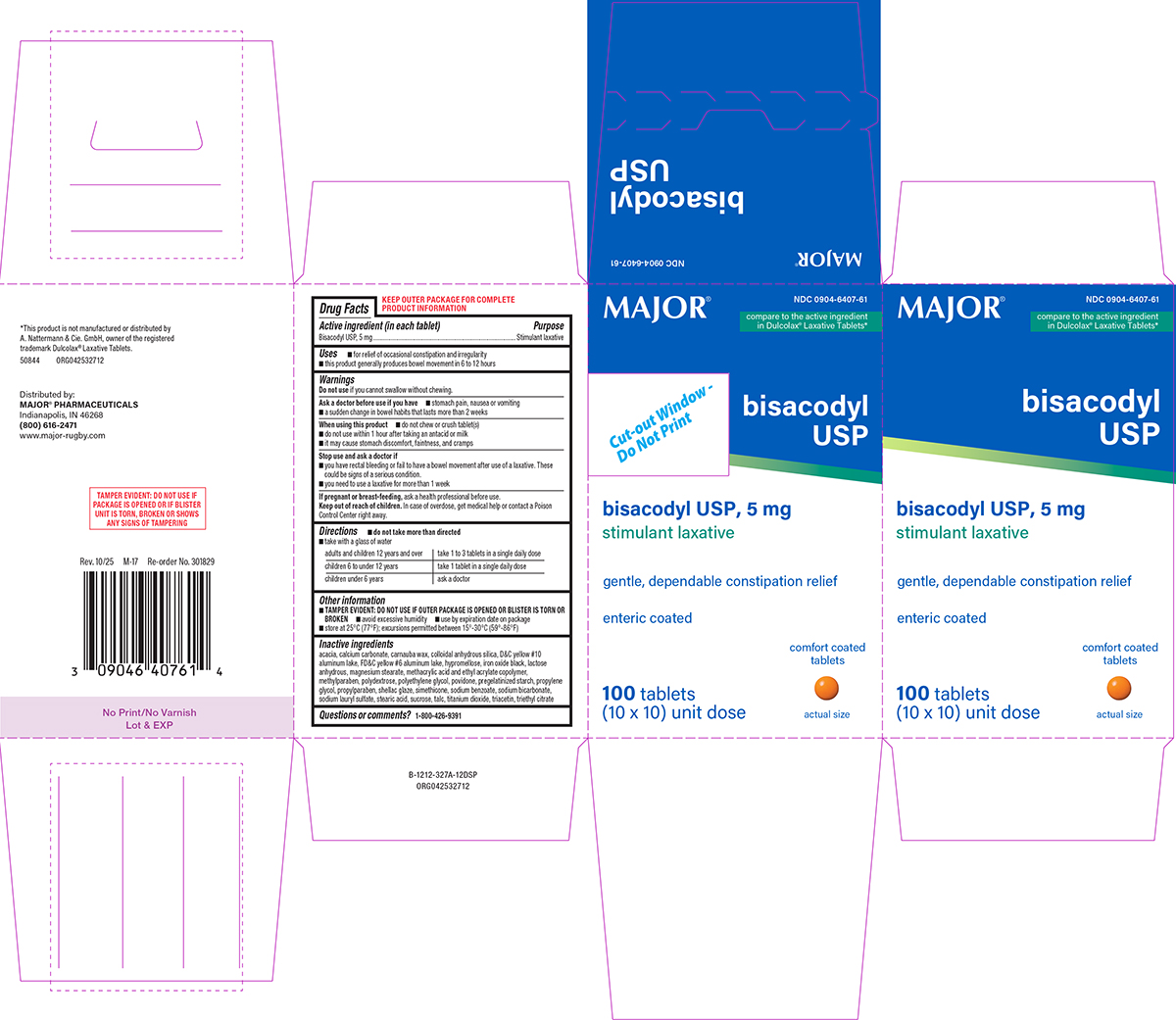 DRUG LABEL: Bisacodyl
NDC: 0904-6407 | Form: TABLET, DELAYED RELEASE
Manufacturer: Major Pharmaceuticals
Category: otc | Type: HUMAN OTC DRUG LABEL
Date: 20260113

ACTIVE INGREDIENTS: BISACODYL 5 mg/1 1
INACTIVE INGREDIENTS: ACACIA; CALCIUM CARBONATE; CARNAUBA WAX; SILICON DIOXIDE; D&C YELLOW NO. 10 ALUMINUM LAKE; FD&C YELLOW NO. 6 ALUMINUM LAKE; HYPROMELLOSE, UNSPECIFIED; FERROSOFERRIC OXIDE; ANHYDROUS LACTOSE; MAGNESIUM STEARATE; METHACRYLIC ACID AND ETHYL ACRYLATE COPOLYMER; METHYLPARABEN; POLYDEXTROSE; POLYETHYLENE GLYCOL, UNSPECIFIED; POVIDONE, UNSPECIFIED; STARCH, CORN; PROPYLENE GLYCOL; PROPYLPARABEN; SHELLAC; DIMETHICONE; WATER; SODIUM BENZOATE; SODIUM BICARBONATE; SODIUM LAURYL SULFATE; STEARIC ACID; SUCROSE; TALC; TITANIUM DIOXIDE; TRIACETIN; TRIETHYL CITRATE

Major 44-327A-Unit dose

Active ingredient (in each tablet)

Bisacodyl USP, 5 mg

Purpose

Stimulant laxative

Uses

- for relief of occasional constipation and irregularity
- this product generally produces bowel movement in 6 to 12 hours

Warnings

Do not use

if you cannot swallow without chewing.

Ask a doctor before use if you have

- stomach pain, nausea or vomiting
- a sudden change in bowel habits that lasts more than 2 weeks

When using this product

- do not chew or crush tablet(s)
- do not use within 1 hour after taking an antacid or milk
- it may cause stomach discomfort, faintness, and cramps

Stop use and ask a doctor if

- you have rectal bleeding or fail to have a bowel movement after use of a laxative. These could be signs of a serious condition.
- you need to use a laxative for more than 1 week

If pregnant or breast-feeding,

ask a health professional before use.

Keep out of reach of children.

In case of overdose, get medical help or contact a Poison Control Center right away.

Directions

- do not take more than directed
- take with a glass of water

adults and children 12 years and over | take 1 to 3 tablets in a single daily dose
children 6 to under 12 years | take 1 tablet in a single daily dose
children under 6 years | ask a doctor

Other information

- TAMPER EVIDENT: DO NOT USE IF OUTER PACKAGE IS OPENED OR BLISTER IS TORN OR BROKEN
- avoid excessive humidity
- use by expiration date on package
- store at 25°C (77°F); excursions permitted between 15°-30°C (59°-86°F)

Inactive ingredients

acacia, calcium carbonate, carnauba wax, colloidal anhydrous silica, D&C yellow #10 aluminum lake, FD&C yellow #6 aluminum lake, hypromellose, iron oxide black, lactose anhydrous, magnesium stearate, methacrylic acid and ethyl acrylate copolymer, methylparaben, polydextrose, polyethylene glycol, povidone, pregelatinized starch, propylene glycol, propylparaben, shellac glaze, simethicone, sodium benzoate, sodium bicarbonate, sodium lauryl sulfate, stearic acid, sucrose, talc, titanium dioxide, triacetin, triethyl citrate

Questions or comments?

1-800-426-9391

Principal display panel

NDC 0904-6407-61

MAJOR®

compare to the active ingredient
in Dulcolax® Laxative Tablets*

bisacodyl
USP

bisacodyl USP, 5 mg
stimulant laxative

gentle, dependable constipation relief

enteric coated

100 tablets
(10 x 10) unit dose

comfort coated
tablets

actual size

*This product is not manufactured or distributed by
A. Nattermann & Cie. GmbH, owner of the registered
trademark Dulcolax® Laxative Tablets.

TAMPER EVIDENT: DO NOT USE IF
PACKAGE IS OPENED OR IF BLISTER
UNIT IS TORN, BROKEN OR SHOWS
ANY SIGNS OF TAMPERING

50844 ORG042532712

Distributed by:
MAJOR® PHARMACEUTICALS
Indianapolis, IN 46268
(800) 616-2471
www.major-rugby.com

Major 44-327